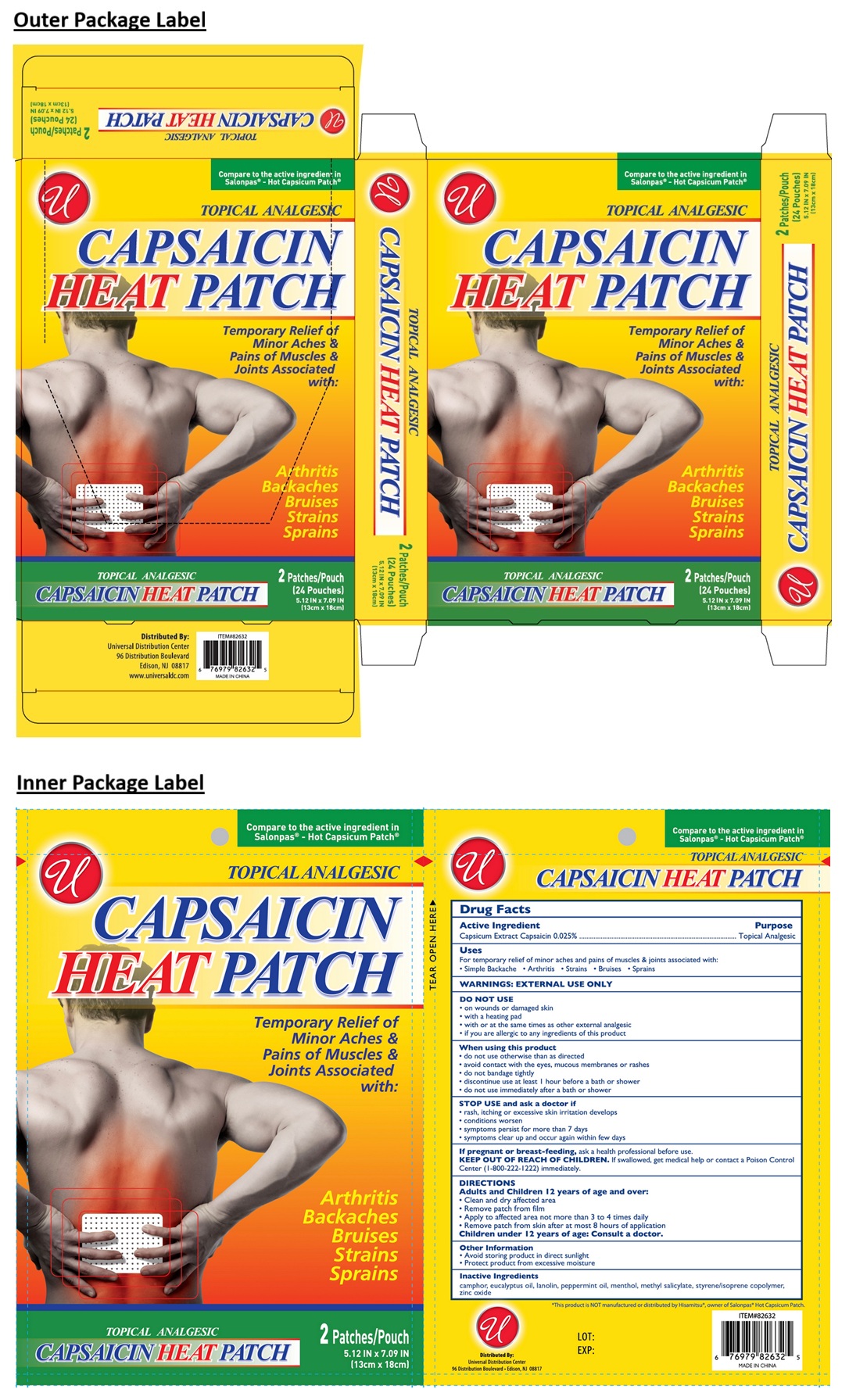 DRUG LABEL: Capsaicin Heat
NDC: 52000-040 | Form: PATCH
Manufacturer: Universal Distribution Center LLC
Category: otc | Type: HUMAN OTC DRUG LABEL
Date: 20250929

ACTIVE INGREDIENTS: CAPSAICIN 0.025 g/100 g
INACTIVE INGREDIENTS: CAMPHOR (SYNTHETIC); EUCALYPTUS OIL; LANOLIN; PEPPERMINT OIL; MENTHOL, UNSPECIFIED FORM; METHYL SALICYLATE; STYRENE/ISOPRENE COPOLYMER (28:72; 210000 MW); ZINC OXIDE

CAPSAICIN HEAT PATCH

Active Ingredient

Capsicum Extract Capsaicin 0.025%

Purpose

Topical Analgesic

Uses

For temporary relief of minor aches and pains of muscles & joints associated with:
• Simple Backache • Arthritis • Strains • Bruises • Sprains

WARNINGS:

EXTERNAL USE ONLY

DO NOT USE
• on wounds or damaged skin
• with a heating pad
• with or at the same times as other external analgesic
• if you are allergic to any ingredients of this product

When using this product
• do not use otherwise than as directed
• avoid contact with the eyes, mucous membranes or rashes
• do not bandage tightly
• discontinue use at least 1 hour before a bath or shower
• do not use immediately after a bath or shower

STOP USE and ask a doctor if
• rash, itching or excessive skin irritation develops
• conditions worsen
• symptoms persist for more than 7 days
• symptoms clear up and occur again within few days

If pregnant or breast-feeding, ask a health professional before use.

KEEP OUT OF REACH OF CHILDREN. If swallowed, get medical help or contact a Poison Control Center (1-800-222-1222) immediately.

DIRECTIONS

Adults and Children 12 years of age and over:

- Clean and dry affected area
- Remove patch from film
- Apply to affected area not more than 3 to 4 times daily
- Remove patch from skin after at most 8 hours of application

Children under 12 years of age: Consult a doctor.

Other Information

• Avoid storing product in direct sunlight
• Protect product from excessive moisture

Inactive Ingredients

camphor, eucalyptus oil, lanolin, peppermint oil, menthol, methyl salicylate, styrene/isoprene copolymer, zinc oxide

Compare to the active ingredient in Salonpas® - Hot Capsicum Patch®

*This product is NOT manufactured or distributed by Hisamitsu®, owner of Salonpas® Hot Capsicum Patch.

Distributed By:

Universal Distribution Center

96 Distribution Boulevard • Edison, NJ 08817

MADE IN CHINA

www.universaldc.com